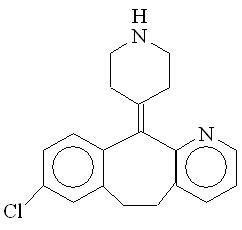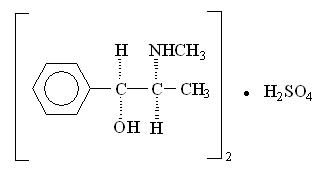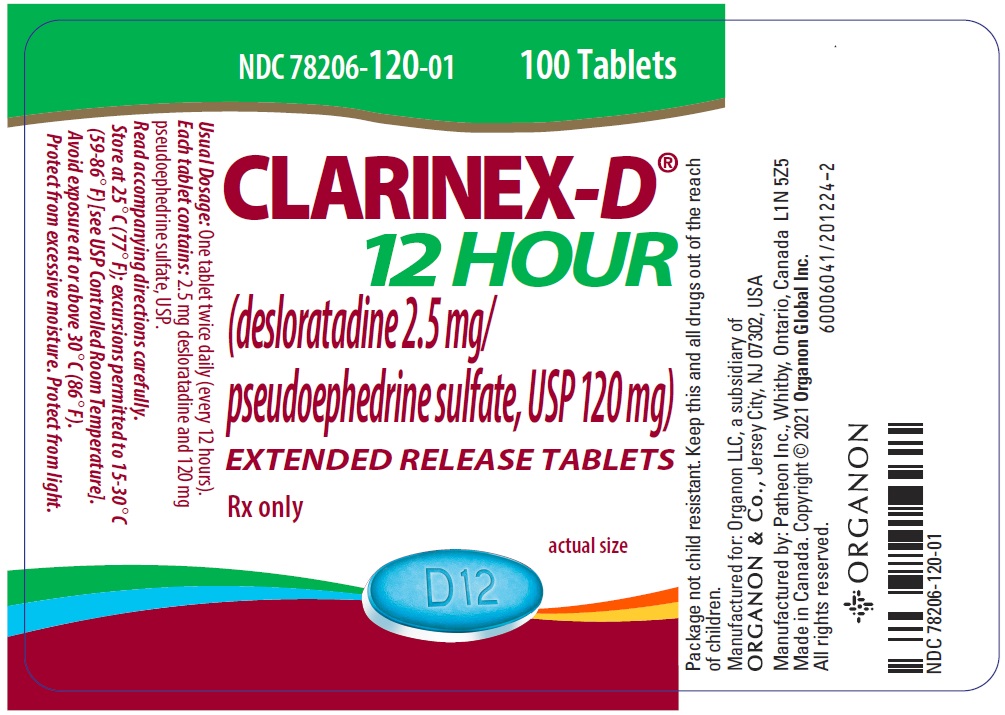 DRUG LABEL: CLARINEX-D 12 HOUR
NDC: 78206-120 | Form: TABLET, EXTENDED RELEASE
Manufacturer: Organon LLC
Category: prescription | Type: HUMAN PRESCRIPTION DRUG LABEL
Date: 20251112

ACTIVE INGREDIENTS: desloratadine 2.5 mg/1 1; pseudoephedrine sulfate 120 mg/1 1
INACTIVE INGREDIENTS: hypromellose, unspecified; microcrystalline cellulose; povidone, unspecified; silicon dioxide; magnesium stearate; starch, corn; edetate disodium; anhydrous citric acid; stearic acid; FD&C Blue No. 2; aluminum oxide

HIGHLIGHTS OF PRESCRIBING INFORMATION

These highlights do not include all the information needed to use CLARINEX-D 12 HOUR Extended Release Tablets safely and effectively. See full prescribing information for CLARINEX-D 12 HOUR Extended Release Tablets.
CLARINEX-D® 12 HOUR Extended Release Tablets (desloratadine/pseudoephedrine sulfate) for oral use
Initial U.S. Approval: 2005

1 INDICATIONS AND USAGE

CLARINEX-D 12 HOUR is a combination product containing a histamine-1 (H1) receptor antagonist and an alpha adrenergic agonist indicated for:

- Relief of nasal and non-nasal symptoms of seasonal allergic rhinitis, including nasal congestion, in adults and adolescents 12 years of age and older. (1.1)

2 DOSAGE AND ADMINISTRATION

For oral use only (2)

Adults and adolescents 12 years of age and over: The recommended dose of CLARINEX-D 12 HOUR Extended Release Tablets is one tablet twice a day. (2.1)

3 DOSAGE FORMS AND STRENGTHS

Desloratadine 2.5 mg/Pseudoephedrine sulfate 120 mg tablets. (3)

4 CONTRAINDICATIONS

- Hypersensitivity (4)
- Narrow-Angle Glaucoma (4)
- Urinary Retention (4)
- Patients Receiving MAO Inhibitors or within 14 days of stopping such treatment (4)
- Severe hypertension or severe coronary artery disease. (4)

5 WARNINGS AND PRECAUTIONS

- Cardiovascular and central nervous system effects: Use with caution in patients with cardiovascular disorders. (5.1)
- Coexisting conditions: Use with caution in patients with increased intraocular pressure, prostatic hypertrophy, diabetes mellitus, or hyperthyroidism. (5.2)

6 ADVERSE REACTIONS

- The most common adverse reactions (reported in ≥2% of patients) were insomnia, headache, mouth dry, fatigue, somnolence, pharyngitis, dizziness, nausea, and anorexia. (6.1)

To report SUSPECTED ADVERSE REACTIONS, contact Organon LLC, a subsidiary of Organon & Co., at 1-844-674-3200 or FDA at 1-800-FDA-1088 or www.fda.gov/medwatch.

7 DRUG INTERACTIONS

Monoamine Oxidase (MAO) Inhibitors: Do not use. May potentiate the effect of pseudoephedrine on vascular system. (7.1)

8 USE IN SPECIFIC POPULATIONS

- Renal impairment: Avoid in patients with renal impairment. (8.6)
- Hepatic impairment: Avoid in patients with hepatic impairment. (8.7)

FULL PRESCRIBING INFORMATION

1 INDICATIONS AND USAGE

1.1 Seasonal Allergic Rhinitis

CLARINEX-D® 12 HOUR Extended Release Tablets is indicated for the relief of the nasal and non-nasal symptoms of seasonal allergic rhinitis, including nasal congestion, in adults and adolescents 12 years of age and older. CLARINEX-D 12 HOUR Extended Release Tablets should be administered when the antihistaminic properties of desloratadine and the nasal decongestant properties of pseudoephedrine are desired [see Clinical Pharmacology (12)].

2 DOSAGE AND ADMINISTRATION

Administer CLARINEX-D 12 HOUR Extended Release Tablet by the oral route only. Do not break, chew, or crush the tablet. Swallow the tablet whole.

2.1 Adults and Adolescents 12 years of Age and Over

The recommended dose of CLARINEX-D 12 HOUR Extended Release Tablets is 1 tablet twice a day, administered approximately 12 hours apart and with or without a meal. Higher doses or increased dosing frequency of CLARINEX-D 12 HOUR Extended Release Tablets have not demonstrated increased effectiveness. Do not exceed the recommended dose as desloratadine and pseudoephedrine, the active components of CLARINEX-D 12 HOUR Extended Release Tablets have been associated with adverse effects at higher doses [see Overdosage (10.1) and (10.2)].

3 DOSAGE FORMS AND STRENGTHS

CLARINEX-D 12 HOUR Extended Release Tablets are oval shaped, blue and white bilayer tablets with "D12" embossed in the blue layer. Each tablet contains 2.5 mg desloratadine in the blue immediate-release layer and 120 mg of pseudoephedrine sulfate USP in the white extended-release layer.

4 CONTRAINDICATIONS

CLARINEX-D 12 HOUR Extended Release Tablets are contraindicated in:

- Patients with hypersensitivity to any of its ingredients, or to loratadine [see Warnings and Precautions (5.4) and Adverse Reactions (6.2)]
- Patients with narrow-angle glaucoma
- Patients with urinary retention
- Patients receiving monoamine oxidase (MAO) inhibitor therapy or within fourteen (14) days of stopping such treatment [see Drug Interactions (7.1)]
- Patients with severe hypertension or severe coronary artery disease

5 WARNINGS AND PRECAUTIONS

5.1 Cardiovascular and Central Nervous System Effects

The pseudoephedrine sulfate contained in CLARINEX-D 12 HOUR Extended Release Tablets, like other sympathomimetic amines, can produce cardiovascular and central nervous system (CNS) effects in some patients such as insomnia, dizziness, weakness, tremor, or arrhythmias. In addition, central nervous system stimulation with convulsions or cardiovascular collapse with accompanying hypotension has been reported. Therefore, CLARINEX-D 12 HOUR Extended Release Tablets should be used with caution in patients with cardiovascular disorders, and should not be used in patients with severe hypertension or severe coronary artery disease.

5.2 Coexisting Conditions

CLARINEX-D 12 HOUR Extended Release Tablets contain pseudoephedrine sulfate, a sympathomimetic amine, and therefore should be used with caution in patients with diabetes and hyperthyroidism. Also use with caution in patients with prostatic hypertrophy or increased intraocular pressure, as urinary retention and narrow-angle glaucoma may occur [see Contraindications (4)].

5.3 Co-Administration with Monoamine Oxidase (MAO) Inhibitors

CLARINEX-D 12 HOUR Extended Release Tablets should not be used in patients receiving monoamine oxidase (MAO) inhibitor therapy or within fourteen (14) days of stopping such treatment as an increase in blood pressure or hypertensive crisis, may occur [see Contraindications (4) and Drug Interactions (7.1)].

5.4 Hypersensitivity Reactions

Hypersensitivity reactions including rash, pruritus, urticaria, edema, dyspnea, and anaphylaxis have been reported after administration of desloratadine a component of CLARINEX-D 12 HOUR Extended Release Tablets. If such a reaction occurs, therapy with CLARINEX-D 12 HOUR Extended Release Tablets should be stopped and alternative treatment should be considered [see Adverse Reactions (6.2)].

5.5 Renal Impairment

CLARINEX-D 12 HOUR Extended Release Tablets should generally be avoided in patients with renal impairment [see Clinical Pharmacology (12.3)].

5.6 Hepatic Impairment

CLARINEX-D 12 HOUR Extended Release Tablets should generally be avoided in patients with hepatic impairment [see Clinical Pharmacology (12.3)].

6 ADVERSE REACTIONS

The following adverse reactions are discussed in greater detail in other sections of the label:

- Cardiovascular and Central Nervous System effects [see Warnings and Precautions (5.1)]
- Increased intraocular pressure [see Warnings and Precautions (5.2)]
- Urinary retention in patients with prostatic hypertrophy [see Warnings and Precautions (5.2)]
- Hypersensitivity reactions [see Warnings and Precautions (5.4)]
- Severe Skin Reactions

6.1 Clinical Trials Experience

Because clinical trials are conducted under widely varying conditions, adverse reaction rates observed in the clinical trials of a drug cannot be directly compared to rates in the clinical trials of another drug and may not reflect the rates observed in clinical practice.

The safety data described below are from 2 clinical trials with CLARINEX-D 12 HOUR Extended Release Tablets that included 1248 patients with seasonal allergic rhinitis, of which 414 patients received CLARINEX-D 12 HOUR Extended Release Tablets twice daily for up to 2 weeks. The majority of patients were between 18 and <65 years of age with a mean age of 35.8 years and were predominantly women (64%). Patient ethnicity was 82% Caucasian, 9% Black, 6% Hispanic and 3% Asian/other ethnicity. The percentage of subjects receiving CLARINEX-D 12 HOUR Extended Release Tablets and who discontinued from the clinical trials because of an adverse event was 3.6%. Adverse reactions that were reported by ≥2% of subjects receiving CLARINEX-D 12 HOUR Extended Release Tablets are shown in Table 1.

Table 1: Incidence of Adverse Reactions Reported by ≥2% of Subjects Receiving CLARINEX-D 12 HOUR Extended Release Tablets
Adverse Reaction | CLARINEX-D 12 HOUR BID (N=414) | Desloratadine 5 mg QD (N=412) | Pseudoephedrine 120 mg BID (N=422)
Gastrointestinal Disorders
Mouth Dry | 8% | 2% | 8%
Nausea | 2% | 1% | 3%
General Disorders and Administration Site Conditions
Fatigue | 4% | 2% | 2%
Metabolism and Nutrition Disorders
Anorexia | 2% | 0% | 2%
Nervous System Disorders
Headache | 8% | 8% | 9%
Somnolence | 3% | 4% | 2%
Dizziness | 3% | 2% | 2%
Psychiatric Disorders
Insomnia | 10% | 3% | 13%
Respiratory, Thoracic, and Mediastinal Disorders
Pharyngitis | 3% | 3% | 3%

There were no relevant differences in adverse reactions for subgroups of patients as defined by gender, age, or race.

6.2 Post-Marketing Experience

In addition to the adverse reactions reported during clinical trials and listed above, adverse events have been identified during post approval use of CLARINEX-D 12 HOUR Extended Release Tablets. Because these events are reported voluntarily from a population of uncertain size, it is not always possible to reliably estimate their frequency or establish a causal relationship to drug exposure.

Adverse events identified from post-marketing surveillance on the use of CLARINEX-D 12 HOUR Extended Release Tablets include:
Cardiac disorders: tachycardia, palpitations
Respiratory, thoracic and mediastinal disorders: dyspnea
Skin and subcutaneous tissue disorders: rash, pruritus

In addition to these events, the following spontaneous adverse events have been reported during the marketing of desloratadine as a single ingredient product:
Nervous system disorders: headache, somnolence, dizziness, psychomotor hyperactivity, movement disorders (including dystonia, tics, and extrapyramidal symptoms), seizures (reported in patients with and without a known seizure disorder)
Immune system disorders: hypersensitivity reactions (such as urticaria, edema and anaphylaxis)
Investigations: elevated liver enzymes including bilirubin
Hepatobiliary disorders: hepatitis
Metabolism and nutrition disorders: increased appetite

Cases of severe skin reactions such as acute generalized exanthematous pustulosis (AGEP) have been reported with pseudoephedrine-containing products.

7 DRUG INTERACTIONS

No specific interaction studies have been conducted with CLARINEX-D 12 HOUR Extended Release Tablets.

7.1 Monoamine Oxidase Inhibitors

CLARINEX-D 12 HOUR Extended Release Tablets should not be used in patients receiving monoamine oxidase (MAO) inhibitor therapy or within fourteen (14) days of stopping such treatment because the action of pseudoephedrine a component of CLARINEX-D 12 HOUR Extended Release tablets on the vascular system may be potentiated by these agents [see Contraindications (4) and Warnings and Precautions (5.3)].

7.2 Beta-Adrenergic Blocking Agents

The antihypertensive effects of beta-adrenergic blocking agents, methyldopa, and reserpine, may be reduced by sympathomimetics such as pseudoephedrine. Exercise caution when using CLARINEX-D 12 HOUR Extended Release Tablets with these agents.

7.3 Digitalis

Increased ectopic pacemaker activity can occur when pseudoephedrine is used concomitantly with digitalis. Exercise caution when using CLARINEX-D 12 HOUR Extended Release Tablets with these agents.

7.4 Inhibitors of Cytochrome P450 3A4

In controlled clinical studies co-administration of desloratadine with ketoconazole, erythromycin, or azithromycin resulted in increased plasma concentrations of desloratadine and 3-hydroxydesloratadine but there were no clinically relevant changes in the safety profile of desloratadine [see Clinical Pharmacology (12.3)].

7.5 Fluoxetine

In controlled clinical studies co-administration of desloratadine with fluoxetine, a selective serotonin reuptake inhibitor (SSRI), resulted in increased plasma concentrations of desloratadine and 3-hydroxydesloratadine but there were no clinically relevant changes in the safety profile of desloratadine [see Clinical Pharmacology (12.3)].

7.6 Cimetidine

In controlled clinical studies co-administration of desloratadine with cimetidine a histamine H2-receptor antagonist resulted in increased plasma concentrations of desloratadine and 3-hydroxydesloratadine but there were no clinically relevant changes in the safety profile of desloratadine [see Clinical Pharmacology (12.3)].

8 USE IN SPECIFIC POPULATIONS

8.1 Pregnancy

Risk Summary

The limited available data with CLARINEX-D 12 HOUR in pregnant women are not sufficient to inform a drug-associated risk for major birth defects and miscarriage. There are no adequate and well-controlled studies of desloratadine and pseudoephedrine in combination in pregnant women. Neither are there animal reproduction studies conducted with the combination of desloratadine and pseudoephedrine or pseudoephedrine alone. Desloratadine given during organogenesis to pregnant rats was not teratogenic at the summed area under the concentration-time curve (AUC)-based exposures of desloratadine and its metabolite approximately 320 times that at the recommended human daily oral dose (RHD) of 5 mg/day. Desloratadine given during organogenesis to pregnant rabbits was not teratogenic at the AUC-based exposures of desloratadine approximately 230 times that at the RHD. Desloratadine given to pregnant rats during organogenesis through lactation resulted in reduced body weight and slow righting reflex of F1 pups at the summed AUC-based exposures of desloratadine and its metabolite approximately 70 times or greater than that at the RHD [see Data].

The estimated background risk of major birth defects and miscarriage for the indicated populations is unknown. In the U.S. general population, the estimated background risk of major birth defects and miscarriage in clinically recognized pregnancies is 2-4% and 15-20%, respectively.

Data

Human Data

Pseudoephedrine

The majority of studies examining the use of pseudoephedrine in pregnancy did not find an association with an increased risk of congenital anomalies. A few case-control studies conducted reported potential associations with isolated congenital disorders. However, several similar studies did not find statistically significant associations. Methodological limitations of these studies included small sample size, selection bias, recall bias, inadequate adjustment for risk factors, residual confounding, exposure misclassification, and lack of information regarding dose and timing of exposure.

Animal Data

No animal reproduction studies were conducted with the combination of desloratadine and pseudoephedrine or pseudoephedrine alone.

Desloratadine

Desloratadine was given orally during organogenesis to pregnant rats at doses of 6, 24 and 48 mg/kg/day (approximately 50, 200 and 320 times the summed AUC-based exposure of desloratadine and its metabolite at the RHD). No fetal malformations were present. Reduced fetal weights and skeletal variations noted at doses of 24 and 48 mg/kg/day were likely secondary to the maternal toxicities of reduced body weight gain and food consumption observed at the same doses. Desloratadine was also given orally during organogenesis to pregnant rabbits at doses of 15, 30 and 60 mg/kg/day (approximately 30, 70 and 230 times the AUC-based exposure of desloratadine at the RHD). No adverse effects to the fetus were noted. Reduced maternal body weight gain was noted in rabbits at 60 mg/kg/day. In a peri- and post-natal development study, desloratadine was given to rats orally during the peri-natal (Gestation Day 6) through lactation periods (Postpartum Day 21) at doses of 3, 9 and 18 mg/kg/day. Reduced body weight and slow righting reflex were reported in F1 pups at doses of 9 mg/kg/day or greater (approximately 70 times or greater than the summed AUC-based exposure of desloratadine and its metabolite at the RHD). Desloratadine had no effect on F1 pup development at 3 mg/kg/day (approximately 10 times the summed AUC-based exposure of desloratadine and its metabolite at the RHD). Maternal toxicities including reduced body weight gain and food consumption were noted at 18 mg/kg/day for F0 dams. F1 offspring were subsequently mated and there was no developmental toxicity for F2 pups observed.

8.2 Lactation

Risk Summary

Desloratadine and pseudoephedrine both pass into breast milk. There are not sufficient data on the effects of desloratadine on the breastfed infant or the effects of desloratadine on milk production. Pseudoephedrine has been reported to decrease milk production [see Data]. Pseudoephedrine has been reported to cause irritability in breastfed infants. The decision should be made whether to discontinue nursing or to discontinue CLARINEX-D 12 HOUR Extended Release Tablets, taking into account the developmental and health benefits of breastfeeding, the nursing mother's clinical need, and any potential adverse effects on the breastfed infant from desloratadine and pseudoephedrine or from the underlying maternal condition.

Data

Human Data

Pseudoephedrine

In a study of eight lactating women, who were 8 to 76 weeks postpartum and received a single dose of 60 mg of pseudoephedrine, the mean 24-hour milk production was reduced by 24%. In the same study, the estimated mean relative infant dose from breast milk (assuming mean milk consumption of 150 mL/kg/day and a maternal dosing regimen of 60 mg pseudoephedrine four times per day) was calculated to be 4.3% of the weight-adjusted maternal dose.

8.3 Females and Males of Reproductive Potential

Infertility

There are no data available on human infertility associated with desloratadine, pseudoephedrine, or the combination. There are no animal fertility studies with the combination or pseudoephedrine alone.

There were no clinically relevant effects of desloratadine on female fertility in rats. A male specific decrease in fertility occurred at an oral desloratadine dose of 12 mg/kg or greater in rats (approximately 65 times the summed AUC-based exposure of desloratadine and its metabolite at the RHD). Male fertility was unaffected at a desloratadine dose of 3 mg/kg (approximately 10 times the summed AUC-based exposure of desloratadine and its metabolite at the RHD). [See Nonclinical Toxicology (13.1).]

8.4 Pediatric Use

CLARINEX-D 12 HOUR Extended Release Tablets are not indicated for use in pediatric patients under 12 years of age.

8.5 Geriatric Use

The number of subjects (n=10) ≥65 years old treated with CLARINEX-D 12 HOUR Extended Release Tablets was too limited to make any formal statistical comparison regarding the efficacy or safety of this drug product in this age group, or to determine whether they respond differently from younger subjects. Other reported clinical experience has not identified differences between the elderly and younger patients, although the elderly are more likely to have adverse reactions to sympathomimetic amines. In general, dose selection for an elderly patient should be cautious, reflecting the greater frequency of decreased hepatic, renal, or cardiac function, and of concomitant disease or other drug therapy [see Clinical Pharmacology (12.3)].

Pseudoephedrine, desloratadine, and their metabolites are known to be substantially excreted by the kidney, and the risk of adverse reactions may be greater in patients with renal impairment. Because elderly patients are more likely to have decreased renal function, care should be taken in dose selection, and it may be useful to monitor the patient for adverse events [see Clinical Pharmacology (12.3)].

8.6 Renal Impairment

No studies with CLARINEX-D 12 HOUR Extended Release Tablets were conducted in subjects with renal impairment.

CLARINEX-D 12 HOUR Extended Release Tablets should generally be avoided in patients with renal impairment [see Warnings and Precautions (5.5) and Clinical Pharmacology (12.3)].

8.7 Hepatic Impairment

No studies with CLARINEX-D 12 HOUR Extended Release Tablets or pseudoephedrine were conducted in subjects with hepatic impairment.

CLARINEX-D 12 HOUR Extended Release Tablets should generally be avoided in patients with hepatic impairment [see Warnings and Precautions (5.6) and Clinical Pharmacology (12.3)].

8.8 Gender

No clinically significant gender-related differences were observed in the pharmacokinetic parameters of desloratadine, 3-hydroxydesloratadine or pseudoephedrine following administration of CLARINEX-D 12 HOUR Extended Release Tablets.

8.9 Race

No studies have been conducted to evaluate the effect of race on the pharmacokinetics of CLARINEX-D 12 HOUR Extended Release Tablets.

9 DRUG ABUSE AND DEPENDENCE

There is no information to indicate that abuse or dependency occurs with CLARINEX or CLARINEX-D 12 HOUR Extended Release Tablets.

10 OVERDOSAGE

In the event of overdose, consider standard measures to remove any unabsorbed drug. Symptomatic and supportive treatment is recommended. Desloratadine and 3-hydroxydesloratadine are not eliminated by hemodialysis.

10.1 Desloratadine

Information regarding acute overdosage with desloratadine is limited to experience from post-marketing adverse event reports and from clinical trials conducted during the development of the CLARINEX product. In the reported cases of overdose, there were no significant adverse events that were attributed to desloratadine. In a dose-ranging trial, at doses of 10 mg and 20 mg/day, somnolence was reported.

In another study, no clinically relevant adverse events were reported in normal male and female volunteers who were given single daily doses of CLARINEX 45 mg for 10 days [see Clinical Pharmacology (12.2)].

10.2 Sympathomimetics

In large doses, sympathomimetics such as pseudoephedrine may give rise to giddiness, headache, nausea, vomiting, sweating, thirst, tachycardia, precordial pain, palpitations, difficulty in micturition, muscle weakness and tenseness, anxiety, restlessness, and insomnia. Many patients can present a toxic psychosis with delusions and hallucinations. Some may develop cardiac arrhythmias, circulatory collapse, convulsions, coma, and respiratory failure.

11 DESCRIPTION

CLARINEX-D 12 HOUR Extended Release Tablets are oval-shaped blue and white bilayer tablets containing 2.5 mg desloratadine in the blue immediate-release layer and 120 mg of pseudoephedrine sulfate USP in the white extended-release layer which is released slowly, allowing for twice-daily administration.

The inactive ingredients contained in CLARINEX-D 12 HOUR Extended Release Tablets are hypromellose USP, microcrystalline cellulose NF, povidone USP, silicon dioxide NF, magnesium stearate NF, corn starch NF, edetate disodium USP, citric acid anhydrous USP, stearic acid NF, and FD&C Blue No. 2 aluminum lake dye.

Desloratadine, 1 of the 2 active ingredients of CLARINEX-D 12 HOUR Extended Release Tablets, is a white to off-white powder that is slightly soluble in water, but very soluble in ethanol and propylene glycol. It has an empirical formula: C19H19ClN2 and a molecular weight of 310.8. The chemical name is 8-chloro-6,11-dihydro-11-(4-piperdinylidene)-5H-benzo[5,6] cyclohepta [1,2-b]pyridine and has the following structure:

Pseudoephedrine sulfate, the other active ingredient of CLARINEX-D 12 HOUR Extended Release Tablets, is the synthetic salt of one of the naturally occurring dextrorotatory diastereomers of ephedrine and is classified as an indirect sympathomimetic amine. Pseudoephedrine sulfate is a colorless hygroscopic crystal or white, hygroscopic crystalline powder, practically odorless, with a bitter taste. It is very soluble in water, freely soluble in alcohol, and sparingly soluble in ether. The empirical formula for pseudoephedrine sulfate is (C10H15NO)2 • H2SO4; the chemical name is benzenemethanol, α-[1-(methylamino) ethyl]-,[S-(R*,R*)]-, sulfate (2:1)(salt); and the chemical structure is:

12 CLINICAL PHARMACOLOGY

12.1 Mechanism of Action

Desloratadine is a long acting tricyclic histamine antagonist with selective H1-receptor histamine antagonist activity. Receptor binding data indicate that at a concentration of 2 to 3 ng/mL (7 nanomolar), desloratadine shows significant interaction with the human histamine H1 receptor. Desloratadine inhibited histamine release from human mast cells in vitro. Results of a radiolabeled tissue distribution study in rats and a radioligand H1-receptor-binding study in guinea pigs showed that desloratadine does not readily cross the blood brain barrier. The clinical significance of this finding is unknown.

Pseudoephedrine sulfate is an orally active sympathomimetic amine and exerts a decongestant action on the nasal mucosa. Pseudoephedrine sulfate is recognized as an effective agent for the relief of nasal congestion due to allergic rhinitis. Pseudoephedrine produces peripheral effects similar to those of ephedrine and central effects similar to, but less intense than, amphetamines. It has the potential for excitatory side effects.

12.2 Pharmacodynamics

Wheal and Flare: Human histamine skin wheal studies following single and repeated 5 mg doses of desloratadine have shown that the drug exhibits an antihistaminic effect by 1 hour; this activity may persist for as long as 24 hours. There was no evidence of histamine-induced skin wheal tachyphylaxis within the desloratadine 5 mg group over the 28-day treatment period. The clinical relevance of histamine wheal skin testing is unknown.

Effects on QTc: In clinical trials for CLARINEX-D 12 HOUR Extended Release Tablets, ECGs were recorded at baseline and endpoint within 1 to 3 hours after the last dose. The majority of ECGs were normal at both baseline and endpoint. No clinically meaningful changes were observed following treatment with CLARINEX-D 12 HOUR Extended Release Tablets for any ECG parameter, including the QTc interval. An increase in the ventricular rate of 7.1 and 6.4 bpm was observed in the CLARINEX-D 12 HOUR Extended Release Tablets and pseudoephedrine groups, respectively, compared to an increase of 3.2 bpm in subjects receiving desloratadine alone. Single daily doses of CLARINEX 45 mg were given to normal male and female volunteers for 10 days.

All ECGs obtained in this study were manually read in a blinded fashion by a cardiologist. In the CLARINEX-treated subjects, there was a mean increase in the maximum heart rate of 9.2 bpm relative to placebo. The QT interval was corrected for heart rate (QTc) by both Bazett's and Fridericia methods. Using the QTc (Bazett), there was a mean increase of 8.1 msec in the CLARINEX-treated subjects relative to placebo. Using QTc (Fridericia) there was a mean increase of 0.4 msec in CLARINEX-treated subjects relative to placebo. No clinically relevant adverse events were reported.

12.3 Pharmacokinetics

Absorption: In a single dose pharmacokinetic study, the mean time to maximum plasma concentrations (Tmax) for desloratadine occurred at approximately 4 to 5 hours post dose and mean peak plasma concentrations (Cmax) and area under the concentration-time curve (AUC) of approximately 1.09 ng/mL and 31.6 ng∙hr/mL, respectively, were observed. In another pharmacokinetic study, food and grapefruit juice had no effect on the bioavailability (Cmax and AUC) of desloratadine.

For pseudoephedrine, the mean Tmax occurred at 6 to 7 hours post dose and mean peak plasma concentrations (Cmax) and area under the concentration-time curve (AUC) of approximately 263 ng/mL and 4588 ng∙hr/mL, respectively, were observed. Food had no effect on the bioavailability (Cmax and AUC) of pseudoephedrine.

Following oral administration of CLARINEX-D 12 HOUR Extended Release Tablets twice daily for 14 days in healthy volunteers, steady-state conditions were reached on Day 10 for desloratadine, 3-hydroxydesloratadine and pseudoephedrine. For desloratadine, mean steady-state peak plasma concentrations (Cmax) and area under the concentration-time curve AUC 0-12 hrs of approximately 1.7 ng/mL and 16 ng∙hr/mL were observed, respectively. For pseudoephedrine, mean steady-state peak plasma concentrations (Cmax) and AUC 0-12 hrs of 459 ng/mL and 4658 ng∙hr/mL were observed.

Distribution: Desloratadine and 3-hydroxydesloratadine are approximately 82% to 87% and 85% to 89%, bound to plasma proteins, respectively. Protein binding of desloratadine and 3-hydroxydesloratadine was unaltered in subjects with impaired renal function.

Metabolism: Desloratadine (a major metabolite of loratadine) is extensively metabolized to 3-hydroxydesloratadine, an active metabolite, which is subsequently glucuronidated. The enzyme(s) responsible for the formation of 3-hydroxydesloratadine have not been identified. Data from clinical trials with desloratadine indicate that a subset of the general population has a decreased ability to form 3-hydroxydesloratadine, and are poor metabolizers of desloratadine. In pharmacokinetic studies (n=3748), approximately 6% of subjects were poor metabolizers of desloratadine (defined as a subject with an AUC ratio of 3-hydroxydesloratadine to desloratadine less than 0.1, or a subject with a desloratadine half-life exceeding 50 hours). These pharmacokinetic studies included subjects between the ages of 2 and 70 years, including 977 subjects aged 2 to 5 years, 1575 subjects aged 6 to 11 years, and 1196 subjects aged 12 to 70 years. There was no difference in the prevalence of poor metabolizers across age groups. The frequency of poor metabolizers was higher in Blacks (17%, n=988) as compared to Caucasians (2%, n=1462) and Hispanics (2%, n=1063). The median exposure (AUC) to desloratadine in the poor metabolizers was approximately 6-fold greater than in the subjects who are not poor metabolizers. Subjects who are poor metabolizers of desloratadine cannot be prospectively identified and will be exposed to higher levels of desloratadine following dosing with the recommended dose of desloratadine. In multidose clinical safety studies, where metabolizer status was prospectively identified, a total of 94 poor metabolizers and 123 normal metabolizers were enrolled and treated with CLARINEX Syrup for 15 to 35 days. In these studies, no overall differences in safety were observed between poor metabolizers and normal metabolizers. Although not seen in these studies, an increased risk of exposure-related adverse events in patients who are poor metabolizers cannot be ruled out.

Pseudoephedrine alone is incompletely metabolized (less than 1%) in the liver by N-demethylation to an inactive metabolite. The drug and its metabolite are excreted in the urine. About 55% to 96% of an administered dose of pseudoephedrine hydrochloride is excreted unchanged in the urine.

Elimination: Following single dose administration of CLARINEX-D 12 HOUR Extended Release Tablets, the mean plasma elimination half-life of desloratadine was approximately 27 hours. In another study, following administration of single oral doses of desloratadine 5 mg, Cmax and AUC values increased in a dose proportional manner following single oral doses between 5 and 20 mg. The degree of accumulation after 14 days of dosing was consistent with the half-life and dosing frequency. A human mass balance study documented a recovery of approximately 87% of the ^14C-desloratadine dose, which was equally distributed in urine and feces as metabolic products. Analysis of plasma 3-hydroxydesloratadine showed similar Tmax and half-life values compared to desloratadine.

The mean elimination half-life of pseudoephedrine is dependent on urinary pH. The elimination half-life is approximately 3 to 6 or 9 to 16 hours when the urinary pH is 5 or 8, respectively.

Geriatric Subjects: Following multiple-dose administration of CLARINEX Tablets, the mean Cmax and AUC values for desloratadine were 20% greater than in younger subjects (< 65 years old). The oral total body clearance (CL/F) when normalized for body weight was similar between the 2 age groups. The mean plasma elimination half-life of desloratadine was 33.7 hr in subjects ≥65 years old. The pharmacokinetics for 3-hydroxydesloratadine appeared unchanged in older vs. younger subjects. These age-related differences are unlikely to be clinically relevant and no dosage adjustment is recommended in elderly patients.

Pediatric Subjects: CLARINEX-D 12 HOUR Extended Release Tablets are not an appropriate dosage form for use in pediatric patients below 12 years of age.

Renally Impaired: Following a single dose of desloratadine 7.5 mg, pharmacokinetics were characterized in subjects with mild (n=7; creatinine clearance 51–69 mL/min/1.73 m^2), moderate (n=6; creatinine clearance 34–43 mL/min/1.73 m^2) and severe (n=6; creatinine clearance 5–29 mL/min/1.73 m^2) renal impairment or hemodialysis dependent (n=6) subjects. In subjects with mild and moderate renal impairment, median Cmax and AUC values increased by approximately 1.2- and 1.9-fold, respectively, relative to subjects with normal renal function. In subjects with severe renal impairment or who were hemodialysis dependent, Cmax and AUC values increased by approximately 1.7- and 2.5-fold, respectively. Minimal changes in 3-hydroxydesloratadine concentrations were observed. Desloratadine and 3-hydroxydesloratadine were poorly removed by hemodialysis. Plasma protein binding of desloratadine and 3-hydroxydesloratadine was unaltered by renal impairment.

Pseudoephedrine is primarily excreted unchanged in the urine as unchanged drug with the remainder apparently being metabolized in the liver. Therefore, pseudoephedrine may accumulate in patients with renal impairment.

Hepatically Impaired: Following a single oral dose of desloratadine, pharmacokinetics were characterized in subjects with mild (n=4), moderate (n=4) and severe (n=4) hepatic impairment as defined by the Child-Pugh classification of hepatic impairment and 8 subjects with normal hepatic function. Subjects with hepatic impairment, regardless of severity, had approximately a 2.4-fold increase in AUC as compared with normal subjects. The apparent oral clearance of desloratadine in subjects with mild, moderate, and severe hepatic impairment was 37%, 36%, and 28% of that in normal subjects, respectively. An increase in the mean elimination half-life of desloratadine in subjects with hepatic impairment was observed. For 3-hydroxydesloratadine, the mean Cmax and AUC values for subjects with hepatic impairment combined were not statistically significantly different from subjects with normal hepatic function.

Gender: Female subjects treated for 14 days with CLARINEX Tablets had 10% and 3% higher desloratadine Cmax and AUC values, respectively, compared with male subjects. The 3-hydroxydesloratadine Cmax and AUC values were also increased by 45% and 48%, respectively, in females compared with males. However, these apparent differences are not considered to be clinically relevant.

Race: Following 14 days of treatment with CLARINEX Tablets, the Cmax and AUC values for desloratadine were 18% and 32% higher, respectively in Blacks compared with Caucasians. For 3-hydroxydesloratadine there was a corresponding 10% reduction in Cmax and AUC values in Blacks compared to Caucasians. These differences are not considered to be clinically relevant.

Drug Interaction: In 2 controlled crossover clinical pharmacology studies in healthy male (n=12 in each study) and female (n=12 in each study) subjects, desloratadine 7.5 mg (1.5 times the daily dose) once daily was co-administered with erythromycin 500 mg every 8 hours or ketoconazole 200 mg every 12 hours for 10 days. In 3 separate controlled, parallel group clinical pharmacology studies, desloratadine at the clinical dose of 5 mg has been co-administered with azithromycin 500 mg followed by 250 mg once daily for 4 days (n=18) or with fluoxetine 20 mg once daily for 7 days after a 23-day pretreatment period with fluoxetine (n=18) or with cimetidine 600 mg every 12 hours for 14 days (n=18) under steady state conditions to healthy male and female subjects. Although increased plasma concentrations (Cmax and AUC 0-24 hrs) of desloratadine and 3-hydroxydesloratadine were observed (see Table 2), there were no clinically relevant changes in the safety profile of desloratadine, as assessed by electrocardiographic parameters (including the corrected QT interval), clinical laboratory tests, vital signs and adverse events.

Table 2: Changes in Desloratadine and 3-hydroxydesloratadine Pharmacokinetics in Healthy Male and Female Subjects
 | Desloratadine |  | 3-hydroxydesloratadine
 | Cmax | AUC 0-24hrs | Cmax | AUC 0-24hrs
Erythromycin (500 mg Q8h) | +24% | +14% | +43% | +40%
Ketoconazole (200 mg Q12h) | +45% | +39% | +43% | +72%
Azithromycin (500 mg Day 1, 250 mg QD × 4 days) | +15% | +5% | +15% | +4%
Fluoxetine (20 mg QD) | +15% | +0% | +17% | +13%
Cimetidine (600 mg Q12h) | +12% | +19% | -11% | -3%

13 NONCLINICAL TOXICOLOGY

13.1 Carcinogenesis, Mutagenesis, Impairment of Fertility

There are no animal or laboratory studies on the combination product of desloratadine and pseudoephedrine sulfate or pseudoephedrine alone to evaluate carcinogenesis, mutagenesis, or impairment of fertility.

Carcinogenicity Studies:

Desloratadine

The carcinogenic potential of desloratadine was assessed using a loratadine study in rats and a desloratadine study in mice. In a 2-year study in rats, loratadine was administered in the diet at doses up to 25 mg/kg/day (approximately 45 times the summed AUC-based exposure of desloratadine and its metabolite at the RHD). A significantly higher incidence of hepatocellular tumors (combined adenomas and carcinomas) was observed in males given 10 mg/kg/day of loratadine (approximately 10 times the summed AUC-based exposure of desloratadine and its metabolite at the RHD) and in males and females given 25 mg/kg/day of loratadine. The clinical significance of these findings during long-term use of desloratadine is not known. In a 2-year dietary study in mice, males and females given up to 16 mg/kg/day and 32 mg/kg/day desloratadine, respectively (approximately 30 and 70 times the summed AUC-based exposure of desloratadine and its metabolite at the RHD, respectively), did not show significant increases in the incidence of any tumors.

Pseudoephedrine

The carcinogenic potential of pseudoephedrine was assessed using ephedrine sulfate studies in F344/N rats and B6C3F1 mice conducted under the National Toxicology Program (NTP). In a 2-year dietary study in rats, male and female rats given up to 9 and 11 mg/kg/day ephedrine sulfate (approximately 0.4 and 0.5 times the RHD of 240 mg/day on a mg/m^2 basis, respectively) did not show any evidence of tumorigenicity. In a 2-year dietary study in mice, male and female mice given up to 29 and 25 mg/kg/day ephedrine sulfate (approximately 0.7 and 0.6 times the RHD of pseudoephedrine on a mg/m^2 basis, respectively) did not show any evidence of tumorigenicity.

Genotoxicity Studies:

Desloratadine

In genotoxicity studies with desloratadine, there was no evidence of genotoxic potential in a reverse mutation assay (Salmonella/E. coli mammalian microsome bacterial mutagenicity assay) or in 2 assays for chromosomal aberrations (human peripheral blood lymphocyte clastogenicity assay and mouse bone marrow micronucleus assay).

Pseudoephedrine

Mutagenicity studies with pseudoephedrine have not been conducted.

Impairment of Fertility:

Desloratadine

In a female fertility study, desloratadine was given to female rats orally 14 days prior to and throughout mating until Gestation Day 7 at doses of 6, 12 and 24 mg/kg/day. An increase in preimplantation loss and a decrease in number of implantations and fetuses noted at 24 mg/kg (approximately 200 times the summed AUC-based exposure of desloratadine and its metabolite at the RHD) was likely due to maternal toxicities including reduced body weight gain and food consumption. In a male fertility study in rats, desloratadine was given orally to male rats for 70 days prior to mating and throughout the mating period (total dosing period 106-108 days) at doses of 3, 12 and 40 mg/kg/day. Reduced body weight gain, food consumption, and absolute organ weights of testes, epididymis, and cauda epididymis were noted at 40 mg/kg/day. A male-specific decrease in fertility, demonstrated by reduced female conception rates, decreased sperm numbers and motility, and histopathologic changes in testes and epididymis, occurred at a dose of 12 mg/kg or greater (approximately 65 times or greater than the summed AUC-based exposure of desloratadine and its metabolite at the RHD). Desloratadine had no effect on male fertility in rats at 3 mg/kg/day (approximately 10 times the summed AUC-based exposure of desloratadine and its metabolite at the RHD).

Pseudoephedrine

Fertility studies with pseudoephedrine have not been conducted.

14 CLINICAL STUDIES

14.1 Seasonal Allergic Rhinitis

The clinical efficacy and safety of CLARINEX-D 12 HOUR Extended Release Tablets was evaluated in two 2-week multicenter, randomized parallel group clinical trials involving 1248 subjects 12 to 78 years of age with seasonal allergic rhinitis, 414 of whom received CLARINEX-D 12 HOUR Extended Release Tablets. In the 2 trials, subjects were randomized to receive CLARINEX-D 12 HOUR Extended Release Tablets twice daily, CLARINEX Tablets 5 mg once daily, or sustained-release pseudoephedrine tablet 120 mg twice daily for 2 weeks. The majority of patients were between 18 and <65 years of age with a mean age of 35.8 years and were predominantly women (64%). Patient ethnicity was 82% Caucasian, 9% Black, 6% Hispanic and 3% Asian/other ethnicity. Primary efficacy variable was twice-daily reflective patient scoring of 4 nasal symptoms (rhinorrhea, nasal stuffiness/congestion, nasal itching, and sneezing) and four non-nasal symptoms (itching/burning eyes, tearing/watering eyes, redness of eyes, and itching of ears/palate) on a 4 point scale (0=none, 1=mild, 2=moderate, and 3=severe). In both trials, the antihistaminic efficacy of CLARINEX-D 12 HOUR Extended Release Tablets, as measured by total symptom score excluding nasal congestion, was significantly greater than pseudoephedrine alone over the 2-week treatment period; and the decongestant efficacy of CLARINEX-D 12 HOUR Extended Release Tablets, as measured by nasal stuffiness/congestion, was significantly greater than CLARINEX (desloratadine alone) over the 2-week treatment period. Primary efficacy variable results from 1 of 2 trials are shown in Table 3.

Table 3: Changes in Symptoms in a 2-Week Clinical Trial in Subjects With Seasonal Allergic Rhinitis
Treatment Group (n) | Mean Baseline [To qualify at Baseline, the sum of the twice-daily diary reflective scores for the 3 days prior to Baseline and the morning of the Baseline visit were to total ≥42 for total nasal symptom score (sum of 4 nasal symptoms of rhinorrhea, nasal stuffiness/congestion, nasal itching, and sneezing) and a total of ≥35 for total non-nasal symptoms score (sum of 4 non-nasal symptoms of itching/burning eyes, tearing/watering eyes, redness of eyes, and itching of ears/palate), and a score of ≥14 for each of the individual symptoms of nasal stuffiness/congestion and rhinorrhea. Each symptom was scored on a 4-point severity scale (0=none, 1=mild, 2=moderate, 3=severe).] (SEM) | Change (% Change) from Baseline [Mean reduction in score averaged over the 2-week treatment period.] (SEM) | CLARINEX-D 12 HOUR Comparison to Components [The comparison of interest is shown bolded.] (P-value)
Total Symptom Score (Excluding Nasal Congestion)
CLARINEX-D 12 HOUR Extended Release Tablets BID (199) | 14.18 (0.21) | -6.54 (-46.0) (0.30) | -
Pseudoephedrine tablet 120 mg BID (197) | 14.06 (0.21) | -5.07 (-35.9) (0.30) | P<0.001
CLARINEX 5 mg Tablets QD (197) | 14.82 (0.21) | -5.09 (-33.5) (0.30) | P<0.001
Nasal Stuffiness/Congestion
CLARINEX-D 12 HOUR Extended Release Tablets BID (199) | 2.47 (0.027) | -0.93 (-37.4) (0.046) | -
Pseudoephedrine tablet 120 mg BID (197) | 2.46 (0.027) | -0.75 (-31.2) (0.046) | P=0.006
CLARINEX 5 mg Tablets QD (197) | 2.50 (0.027) | -0.66 (-26.7) (0.046) | P<0.001
SEM=Standard Error of the Mean

There were no significant differences in the efficacy of CLARINEX-D 12 HOUR Extended Release Tablets across subgroups of subjects defined by gender, age, or race.

16 HOW SUPPLIED/STORAGE AND HANDLING

CLARINEX-D 12 HOUR Extended Release Tablets are oval-shaped, blue and white bilayer tablets with "D12" embossed in the blue layer, containing 2.5 mg desloratadine in the blue immediate-release layer and 120 mg of pseudoephedrine sulfate USP in the white extended-release layer. CLARINEX-D 12 HOUR Extended Release Tablets are supplied in high-density polyethylene bottles of 100 (NDC 78206-120-01).

STORAGE AND HANDLING

Storage: Store at 25°C (77°F); excursions permitted to 15°–30°C (59°–86°F) [see USP Controlled Room Temperature]. Avoid exposure at or above 30°C (86°F). Protect from excessive moisture. Protect from light.

17 PATIENT COUNSELING INFORMATION

Advise the patient to read the FDA-approved patient labeling (Patient Information).

17.1 Cardiovascular and Central Nervous System Effects

Patients should be informed that pseudoephedrine, one of the active ingredients in CLARINEX-D 12 HOUR Extended Release Tablets may cause cardiovascular or central nervous system effects such as insomnia, dizziness, tremor, convulsions or arrhythmia.

17.2 Dosing

Patients should be advised not to increase the dose or dosing frequency of CLARINEX-D 12 HOUR Extended Release Tablets.

17.3 Additional Antihistamines and/or Decongestants

Patients should be advised against the concurrent use of CLARINEX-D 12 HOUR Extended Release Tablets with other antihistamines and/or decongestants.

17.4 Monoamine Oxidase (MAO) Inhibitors

Patients should be informed that due to its pseudoephedrine component, they should not use CLARINEX-D 12 HOUR with a monoamine oxidase (MAO) inhibitor or within 14 days of stopping use of an MAO inhibitor.

17.5 Coexisting Conditions

Patients with severe hypertension or severe coronary artery disease, narrow-angle glaucoma, or urinary retention should be advised not to use CLARINEX-D 12 HOUR Extended Release Tablets.

17.6 Instructions for Use

Patients should be instructed not to break, crush, or chew the tablet; the tablet should be swallowed whole, and can be taken without regard to meals.

Manufactured for: Organon LLC, a subsidiary of
ORGANON & Co.,
Jersey City, NJ 07302, USA

For patent information: www.organon.com/our-solutions/patent/

Copyright © 2021 Organon Global Inc.
All rights reserved.

uspi-og4117a-t-d12-2106r000

PATIENT INFORMATION

CLARINEX-D® (CLA-RI-NEX) 12 Hour Extended Release Tablets
(desloratadine and pseudoephedrine sulfate)

Read the Patient Information that comes with CLARINEX-D 12 Hour Extended Release Tablets before you start taking it and each time you get a refill. There may be new information. This leaflet is a summary of the information for patients. Your doctor or pharmacist can give you additional information. This leaflet does not take the place of talking to your doctor about your medical condition or treatment.

What is CLARINEX-D® 12 Hour Extended Release Tablets?

CLARINEX-D 12 Hour Extended Release Tablets is a prescription medicine that contains the medicines desloratadine (an antihistamine) and pseudoephedrine (a nasal decongestant). CLARINEX-D 12 Hour Extended Release Tablets is used to help control the symptoms of seasonal allergic rhinitis (sneezing, stuffy nose, runny nose and itching of the nose) in adults and children 12 years and older.

CLARINEX-D 12 Hour Extended Release Tablets is not for children under 12 years of age.

Who should not take CLARINEX-D® 12 Hour Extended Release Tablets?

Do not take CLARINEX-D 12 Hour Extended Release Tablets if you:

- are allergic to desloratadine or pseudoephedrine sulfate or any of the ingredients in CLARINEX-D 12 Hour Extended Release Tablets. See the end of this leaflet for a complete list of ingredients in CLARINEX-D 12 Hour Extended Release Tablets.
- are allergic to loratadine (Alavert, Claritin)
- have narrow-angle glaucoma
- have problems with urination (urinary retention)
- take a Monoamine Oxidase Inhibitor (MAOI) medicine to treat depression, or if you stopped taking an MAOI medicine within the last 2 weeks. Ask your doctor or pharmacist if you are not sure if you take an MAOI medicine.
- have severe high blood pressure
- have severe heart disease

Talk to your doctor before taking this medicine if you have any of these conditions.

What should I tell my doctor before taking CLARINEX-D® 12 Hour Extended Release Tablets?

Before you take CLARINEX-D 12 Hour Extended Release Tablets, tell your doctor if you:

- have any of the conditions listed in the section "Who should not take CLARINEX-D 12 Hour Extended Release Tablets?"
- diabetes
- hyperthyroidism
- have prostate problems
- have liver or kidney problems
- have any other medical conditions
- are pregnant or plan to become pregnant. It is not known if CLARINEX-D 12 Hour Extended Release Tablets will harm your unborn baby. Talk to your doctor if you are pregnant or plan to become pregnant.
- are breastfeeding or plan to breastfeed. CLARINEX-D 12 Hour Extended Release Tablets can pass into your breast milk. Talk to your doctor about the best way to feed your baby if you take CLARINEX-D 12 Hour Extended Release Tablets.

Tell your doctor about all the medicines you take, including prescription and nonprescription medicines, vitamins and herbal supplements. CLARINEX-D® 12 Hour Extended Release Tablets may affect the way other medicines work, and other medicines may affect how CLARINEX-D 12 Hour Extended Release Tablets works. Especially tell your doctor if you take:

- Monoamine Oxidase Inhibitors (MAOIs). You should not use CLARINEX-D 12 Hour Extended Release Tablets if you take an MAOI or within 2 weeks of stopping an MAOI.
- methyldopa
- reserpine (Serpalan)
- digitalis (Digoxin, Lanoxicaps, Lanoxin) ketoconazole (Nizoral)
- erythromycin (Ery-tab, Eryc, PCE)
- azithromycin (Zithromax, Zmax)
- antihistamines
- other decongestant medicines

Know the medicines you take. Keep a list of your medicines and show it to your doctor and pharmacist when you get a new medicine.

How should I take CLARINEX-D® 12 Hour Extended Release Tablets?

Take CLARINEX-D 12 Hour Extended Release Tablets exactly as your doctor tells you to take it.

- CLARINEX-D 12 Hour Extended Release Tablets can be taken with or without food.
- Swallow CLARINEX-D 12 Hour Extended Release Tablets whole. Do not break, crush, or chew CLARINEX-D 12 Hour Extended Release Tablets before swallowing. If you cannot swallow CLARINEX-D 12 Hour Extended Release Tablets whole, tell your doctor. You may need a different medicine.
- Take 1 CLARINEX-D 12 Hour Extended Release Tablet 2 times a day (every 12 hours).

What are the possible side effects of CLARINEX-D® 12 Hour Extended Release Tablets?

CLARINEX-D 12 Hour Extended Release Tablets may cause serious side effects, including:

- Cardiovascular and central nervous system effects, such as
  - unable to sleep (insomnia)
  - dizziness
  - weakness
  - tremor
  - irregular heart beat
  - seizure
  - low blood pressure
- Increased sleepiness or tiredness can happen if you take more CLARINEX-D 12 Hour Extended Release Tablets than your doctor prescribed to you.
- Allergic reactions. Stop taking CLARINEX-D 12 Hour Extended Release Tablets and call your doctor right away or get emergency help if you have any of these symptoms:
  - rash
  - itching
  - hives
  - swelling of your lips, tongue, face, and throat
  - shortness of breath or trouble breathing
- Severe skin reactions including signs and symptoms such as fever, reddening of the skin, or many small pimples

The most common side effects of CLARINEX-D 12 HOUR Extended Release Tablets include:

- unable to sleep (insomnia)
- sore throat
- headache
- dizziness
- dry mouth
- nausea
- tiredness
- loss of appetite
- sleepiness

Tell your doctor if you have any side effect that bothers you or that does not go away.

These are not all of the possible side effects of CLARINEX-D 12 Hour Extended Release Tablets. For more information, ask your doctor or pharmacist.

Call your doctor for medical advice about side effects. You may report side effects to FDA at 1-800-FDA-1088.

How should I store CLARINEX-D® 12 Hour Extended Release Tablets?

- Store CLARINEX-D 12 Hour Extended Release Tablets at 59°F to 86°F (15°C to 30°C)
- Keep CLARINEX-D 12 Hour Extended Release Tablets dry and out of the light.

Keep CLARINEX-D 12 Hour Extended Release Tablets and all medicines out of the reach of children.

General information about CLARINEX-D® 12 Hour Extended Release Tablets

Medicines are sometimes prescribed for purposes other than those listed in a patient information leaflet. Do not use CLARINEX-D 12 Hour Extended Release Tablets for a condition for which it was not prescribed. Do not give CLARINEX-D 12 Hour Extended Release Tablets to other people, even if they have the same condition you have. It may harm them.

This patient information leaflet summarizes the most important information about CLARINEX-D 12 Hour Extended Release Tablets. If you would like more information, talk with your doctor. You can ask your pharmacist or doctor for information about CLARINEX-D 12 Hour Extended Release Tablets that is written for health professionals.

What are the ingredients in CLARINEX-D® 12 Hour Extended Release Tablets?

Active ingredients: desloratadine and pseudoephedrine sulfate

Inactive ingredients: hypromellose USP, microcrystalline cellulose NF, povidone USP, silicon dioxide NF, magnesium stearate NF, corn starch NF, edetate disodium USP, citric acid anhydrous USP, stearic acid NF, and FD&C Blue No. 2 aluminum lake dye.

Manufactured for: Organon LLC, a subsidiary of
ORGANON & Co.,
Jersey City, NJ 07302, USA

For patent information: www.organon.com/our-solutions/patent/

The trademarks depicted herein are owned by their respective companies.

Copyright © 2021 Organon Global Inc.
All rights reserved.

Revised: 6/2021

usppi-og4117a-t-d12-2106r000

PRINCIPAL DISPLAY PANEL - 100 Tablet Bottle Label

NDC 78206-120-01
100 Tablets

CLARINEX-D®
12 HOUR
(desloratadine 2.5 mg/
pseudoephedrine sulfate, USP 120 mg)

EXTENDED RELEASE TABLETS

Rx only

actual size
D12